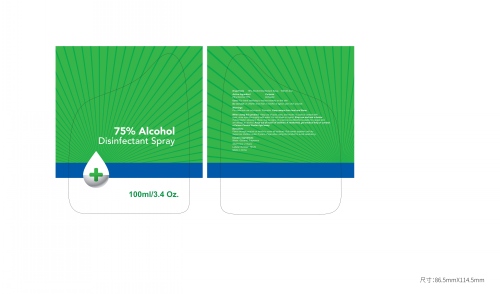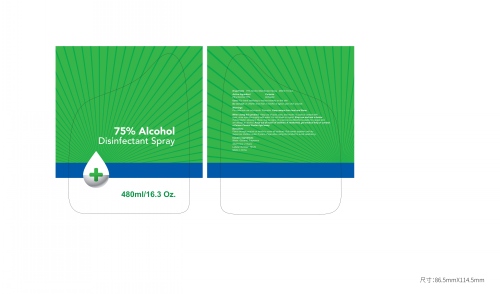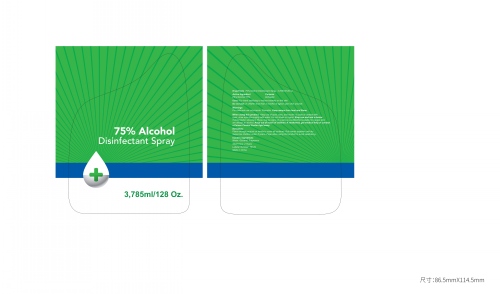 DRUG LABEL: 75% Alcohol Disinfectant
NDC: 75129-013 | Form: SPRAY
Manufacturer: Shanghai Rayshine ENVI-TECH Developing CO., Ltd.
Category: otc | Type: HUMAN OTC DRUG LABEL
Date: 20200524

ACTIVE INGREDIENTS: ALCOHOL 75 mL/100 mL
INACTIVE INGREDIENTS: WATER; GLYCERIN

Alcohol Disinfectant Spray

Active Ingredient

Ethyl Alcohol 75%

Purpose

Antiseptic

Uses

For hand sanitizing to reduce bacteria on the skin.

Warnings

For extermal use only-hands. Flamable. Keep aways from heat and flame.

Do not use

in children less than 2 months of ageon open skin wounds

When using this product

Keep out of eyes,ears,and mouth. In case of contact with eyes, rinse eyes thoroughly with water. Do not inhale or ingest. Stop use and ask a doctor if skinimitation develops.These may be signs of a serious conditionNot suitable for people who are allergic to alcohol. Keep out of reach of children. If swallowed, get medical help or contact
a Poison Control Center right away.

Directions

Place enough product on hands to cover all surfaces. Rub hands together until dry.
Supervise children under 6 years of age when using this product to avoid swallowing.

Inactive ingredients

Water,Glycerol,Fragrance